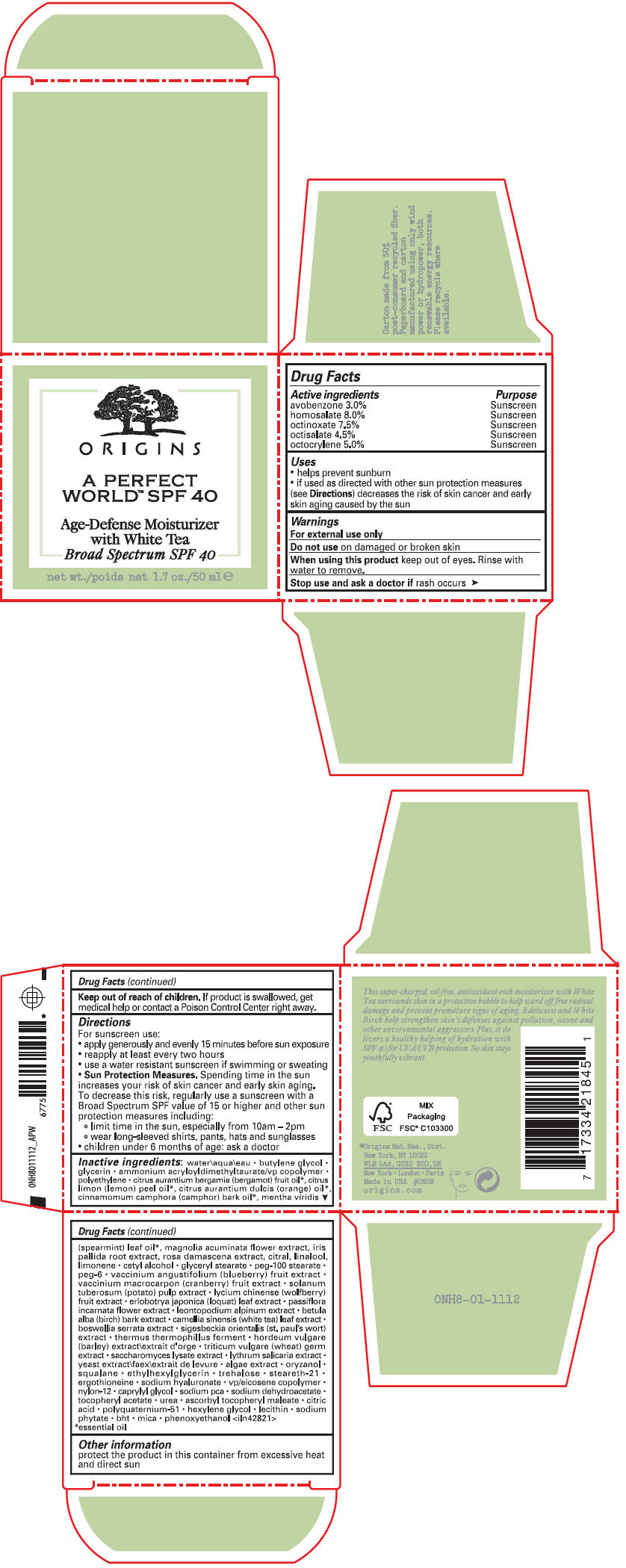 DRUG LABEL: A PERFECT WORLD SPF 40 AGE DEFENSE BROAD SPECTRUM MOISTURIZER WITH WHITE TEA
NDC: 59427-010 | Form: CREAM
Manufacturer: ORIGINS NATURAL RESOURCES INC.
Category: otc | Type: HUMAN OTC DRUG LABEL
Date: 20231201

ACTIVE INGREDIENTS: AVOBENZONE 30 mg/1 mL; HOMOSALATE 80 mg/1 mL; OCTINOXATE 75 mg/1 mL; OCTISALATE 45 mg/1 mL; OCTOCRYLENE 50 mg/1 mL
INACTIVE INGREDIENTS: WATER; BUTYLENE GLYCOL; GLYCERIN; AMMONIUM ACRYLOYLDIMETHYLTAURATE/VP COPOLYMER; HIGH DENSITY POLYETHYLENE; BERGAMOT OIL; LEMON OIL, COLD PRESSED; ORANGE OIL, COLD PRESSED; CAMPHOR OIL; SPEARMINT OIL; MAGNOLIA ACUMINATA FLOWER; IRIS PALLIDA ROOT; CITRAL; LINALOOL, (+/-)-; LIMONENE, (+)-; CETYL ALCOHOL; GLYCERYL MONOSTEARATE; PEG-100 STEARATE; POLYETHYLENE GLYCOL 300; LOWBUSH BLUEBERRY; CRANBERRY; POTATO PULP; LYCIUM CHINENSE FRUIT; ERIOBOTRYA JAPONICA LEAF; PASSIFLORA INCARNATA FLOWER; BETULA PUBESCENS BARK; WHITE TEA; INDIAN FRANKINCENSE; THERMUS THERMOPHILUS LYSATE; HORDEUM VULGARE WHOLE; WHEAT GERM; SACCHAROMYCES LYSATE; YEAST, UNSPECIFIED; ORYZANOL; SQUALANE; ETHYLHEXYLGLYCERIN; TREHALOSE; STEARETH-21; ERGOTHIONEINE; HYALURONATE SODIUM; NYLON-12; CAPRYLYL GLYCOL; SODIUM PYRROLIDONE CARBOXYLATE; SODIUM DEHYDROACETATE; .ALPHA.-TOCOPHEROL ACETATE; UREA; ASCORBYL TOCOPHERYL MALEATE; CITRIC ACID MONOHYDRATE; HEXYLENE GLYCOL; PHYTATE SODIUM; BUTYLATED HYDROXYTOLUENE; MICA; PHENOXYETHANOL

A PERFECT WORLD™ SPF 40 AGE DEFENSE BROAD SPECTRUM MOISTURIZER WITH WHITE TEA

Drug Facts

ACTIVE INGREDIENT

Active ingredients | Purpose
avobenzone 3.0% | Sunscreen
homosalate 8.0% | Sunscreen
octinoxate 7.5% | Sunscreen
octisalate 4.5% | Sunscreen
octocrylene 5.0% | Sunscreen

Uses

- helps prevent sunburn
- if used as directed with other sun protection measures (see Directions) decreases the risk of skin cancer and early skin aging caused by the sun

Warnings

For external use only

Do not use on damaged or broken skin

When using this product keep out of eyes. Rinse with water to remove.

Stop use and ask a doctor if rash occurs

Keep out of reach of children. If product is swallowed, get medical help or contact a Poison Control Center right away.

Directions

For sunscreen use:

- apply generously and evenly 15 minutes before sun exposure
- reapply at least every two hours
- use a water resistant sunscreen if swimming or sweating
- Sun Protection Measures. Spending time in the sun increases your risk of skin cancer and early skin aging. To decrease this risk, regularly use a sunscreen with a Broad Spectrum SPF value of 15 or higher and other sun protection measures including:
  - limit time in the sun, especially from 10am – 2pm
  - wear long-sleeved shirts, pants, hats and sunglasses
- children under 6 months of age: ask a doctor

Inactive ingredients

water\aqua\eau • butylene glycol • glycerin • ammonium acryloyldimethyltaurate/vp copolymer • polyethylene • citrus aurantium bergamia (bergamot) fruit oil [essential oil] , citrus limon (lemon) peel oil , citrus aurantium dulcis (orange) oil , cinnamomum camphora (camphor) bark oil , mentha viridis (spearmint) leaf oil , magnolia acuminata flower extract, iris pallida root extract, rosa damascena extract, citral, linalool, limonene • cetyl alcohol • glyceryl stearate • peg-100 stearate • peg-6 • vaccinium angustifolium (blueberry) fruit extract • vaccinium macrocarpon (cranberry) fruit extract • solanum tuberosum (potato) pulp extract • lycium chinense (wolfberry) fruit extract • eriobotrya japonica (loquat) leaf extract • passiflora incarnata flower extract • leontopodium alpinum extract • betula alba (birch) bark extract • camellia sinensis (white tea) leaf extract • boswellia serrata extract • sigesbeckia orientalis (st. paul's wort) extract • thermus thermophillus ferment • hordeum vulgare (barley) extract\extrait d'orge • triticum vulgare (wheat) germ extract • saccharomyces lysate extract • lythrum salicaria extract • yeast extract\faex\extrait de levure • algae extract • oryzanol • squalane • ethylhexylglycerin • trehalose • steareth-21 • ergothioneine • sodium hyaluronate • vp/eicosene copolymer • nylon-12 • caprylyl glycol • sodium pca • sodium dehydroacetate • tocopheryl acetate • urea • ascorbyl tocopheryl maleate • citric acid • polyquaternium-51 • hexylene glycol • lecithin • sodium phytate • bht • mica • phenoxyethanol <iln42821>

Other information

protect the product in this container from excessive heat and direct sun

PRINCIPAL DISPLAY PANEL - 50 ml Jar Carton

ORIGINS

A PERFECT
WORLD™ SPF 40

Age-Defense Moisturizer
with White Tea
Broad Spectrum SPF 40

net wt. 1.7 oz./50 ml e